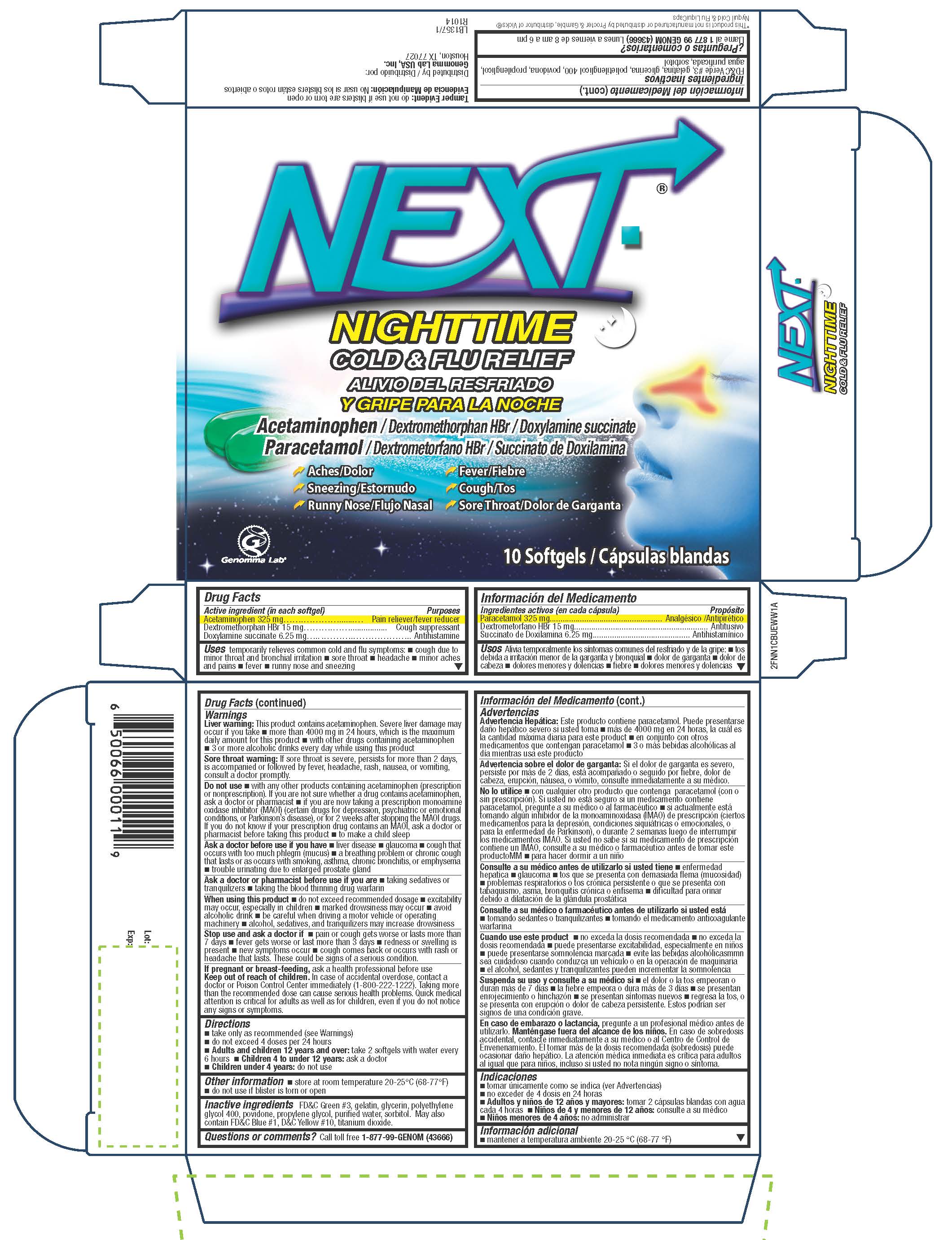 DRUG LABEL: Next Night Time
NDC: 50066-357 | Form: CAPSULE, LIQUID FILLED
Manufacturer: Genomma Lab USA
Category: otc | Type: HUMAN OTC DRUG LABEL
Date: 20150121

ACTIVE INGREDIENTS: ACETAMINOPHEN 325 mg/1 1; DEXTROMETHORPHAN HYDROBROMIDE 15 mg/1 1; DOXYLAMINE SUCCINATE 6.25 mg/1 1
INACTIVE INGREDIENTS: FD&C GREEN NO. 3; GELATIN; GLYCERIN; POLYETHYLENE GLYCOL 400; POVIDONES; PROPYLENE GLYCOL; WATER; SORBITOL

Drug Facts

Active ingredient

Acetaminophen 325 mg
Dextromethorphan HBr 15 mg
Doxylamine succinate 6.25 mg

Purpose

Pain reliever/fever reducer
Cough suppressant
Antihistamine

Uses

temporarily relieves common cold and flu symptoms: cough due to minor throat and bronchial irritation sore throat headache minor aches and pains fever, runny nose and sneezing

Warnings

Liver warning

This product contains acetaminophen. Severe liver damage may occur if you take more than 4 doses in 24 hours, which is the maximum daily amount for this productwith other drugs containing acetaminophen 3 or more alcoholic drinks every day while using this product

Sore throat warning

If sore throat is severe, persists for more than 2 days, is accompanied or followed by fever, headache, rash, nausea, or vomiting, consult a doctor promptly.

Do not use

with any other products containing acetaminophen (prescription or nonprescription). If you are not sure whether a drug contains acetaminophen, ask a doctor or pharmacist if you are now taking a prescription monoamine oxidase inhibitor (MAOI) (certain drugs for depression, psychiatric or emotional conditions, or Parkinson’s disease), or for 2 weeks after stopping the MAOI drugs. If you do not know if your prescription drug contains an MAOI, ask a doctor or pharmacist before taking this product
to make a child sleep

Ask a doctor before use if you have

liver disease glaucoma cough that occurs with too much phlegm (mucus) a breathing problem or chronic cough that lasts or as occurs with smoking, asthma, chronic bronchitis, or emphysema
trouble urinating due to enlarged prostate gland

When using this product

do not exceed recommended dosage excitability may occur, especially in childrenmarked drowsiness may occur avoid alcoholic drink be careful when driving a motor vehicle or operating machinery alcohol, sedatives, and tranquilizers may increase drowsiness

Stop use and ask a doctor if

pain or cough gets worse or lasts more than 7 days fever gets worse or last more than 3 days redness or swelling is present new symptoms occur cough comes back or occurs with rash or headache that lasts. These could be signs of a serious condition.

If pregnant or breast-feeding

ask a health professional before use

Keep Out of Reach of Children

In case of accidental overdose, contact a doctor or Poison Control Center immediately (1-800-222-1222). Taking more than the recommended dose can cause serious health problems. Quick medical attention is critical for adults as well as for children, even if you do not notice any signs or symptoms.

Directions

■ take only as recommended (see Warnings)
■ do not exceed 4 doses per 24 hours
Adults and children 12 years and over: ■ take 2 softgels with water every 6 hours
Children 4 to under 12 years: ■ Ask a doctor
Children under 4 years: ■ Do not use

Other information

store at room temperature do not use if blister is torn or open

Inactive Ingredients

FD&C Green #3, gelatin, glycerin, polyethylene glycol 400, povidone, propylene glycol, purified water, sorbitol. May also contain FD&C Blue #1, D&C Yellow Yellow #10, titanium dioxide.

Questions or comments

Call toll free 1-877-99-GENOM (43666)